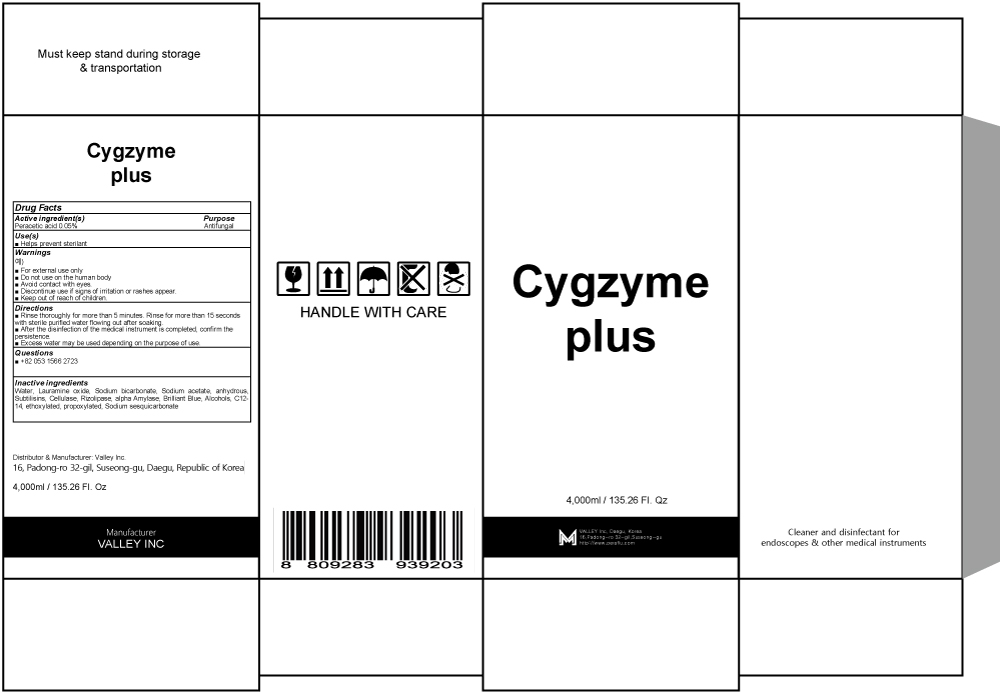 DRUG LABEL: Cygzyme plus
NDC: 81803-050 | Form: LIQUID
Manufacturer: Valley Inc.
Category: otc | Type: HUMAN OTC DRUG LABEL
Date: 20241209

ACTIVE INGREDIENTS: PERACETIC ACID 0.05 g/100 mL
INACTIVE INGREDIENTS: WATER; LAURAMINE OXIDE; SODIUM BICARBONATE; SODIUM ACETATE

ACTIVE INGREDIENT

Peracetic acid 0.05%

INACTIVE INGREDIENTS

Water, Lauramine oxide, Sodium bicarbonate, Sodium acetate, anhydrous, Subtilisins, Cellulase, Rizolipase, alpha Amylase, Brilliant Blue, Alcohols, C12-14, ethoxylated, propoxylated, Sodium sesquicarbonate

PURPOSE

Antifungal

WARNINGS

■ For external use only
■ Do not use on the human body
■ Avoid contact with eyes.
■ Discontinue use if signs of irritation or rashes appear.
■ Keep out of reach of children.

KEEP OUT OF REACH OF CHILDREN

Uses

Helps prevent sterilant

Directions

■ Rinse thoroughly for more than 5 minutes. Rinse for more than 15 seconds with sterile purified water flowing out after soaking.
■ After the disinfection of the medical instrument is completed, confirm the persistence.
■ Excess water may be used depending on the purpose of use.

QUESTIONS

+82 02 1566 2723